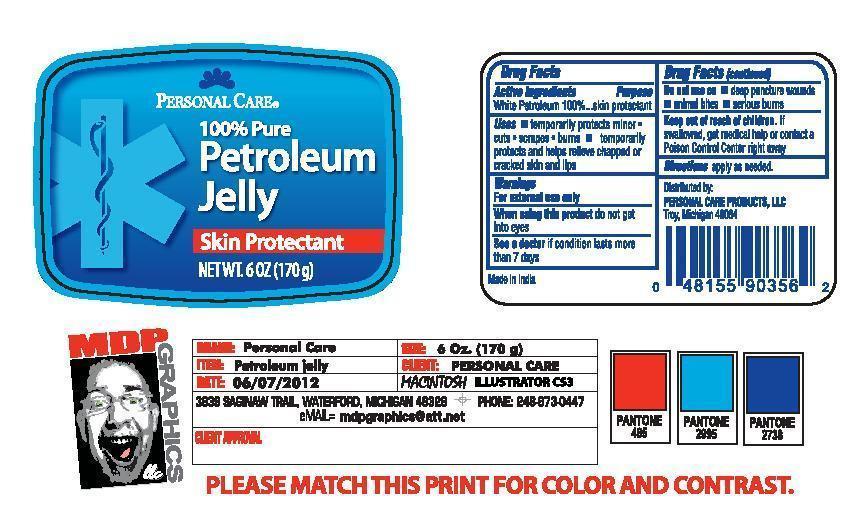 DRUG LABEL: Personal Care Petroleum
NDC: 29500-8010 | Form: JELLY
Manufacturer: PERSONAL CARE PRODUCTS
Category: otc | Type: HUMAN OTC DRUG LABEL
Date: 20120629

ACTIVE INGREDIENTS: PETROLATUM 170 g/170 g
INACTIVE INGREDIENTS: WATER .1 g/170 g

Personal Care Petroleum

Active Ingredients: White Petroleum 100%

Purpose skin protectant

Keep out of reach of children. If swallowed, get medical help or contact a Poison Control Center right away.

Uses

temporarily protects minor cuts, scrapes, burns

temporarily protects and helps relieve chapped or cracked skin and lips

Warnings
For external use only
When using this product do not get into eyes
See a doctor if condition lasts more than 7 days
Do not use on deep puncture wounds, animal bites, serious burns

DOSAGE AND ADMINISTRATION

Directions apply as needed

INACTIVE INGREDIENT

none

PACKAGE LABEL

Personal care

100% Pure Petroleum Jelly

Skin Protectant

Net Wet oz (170 g)

Distributed by:

Personal Care Products, LLC

Troy, Michigan 48084

Made in India